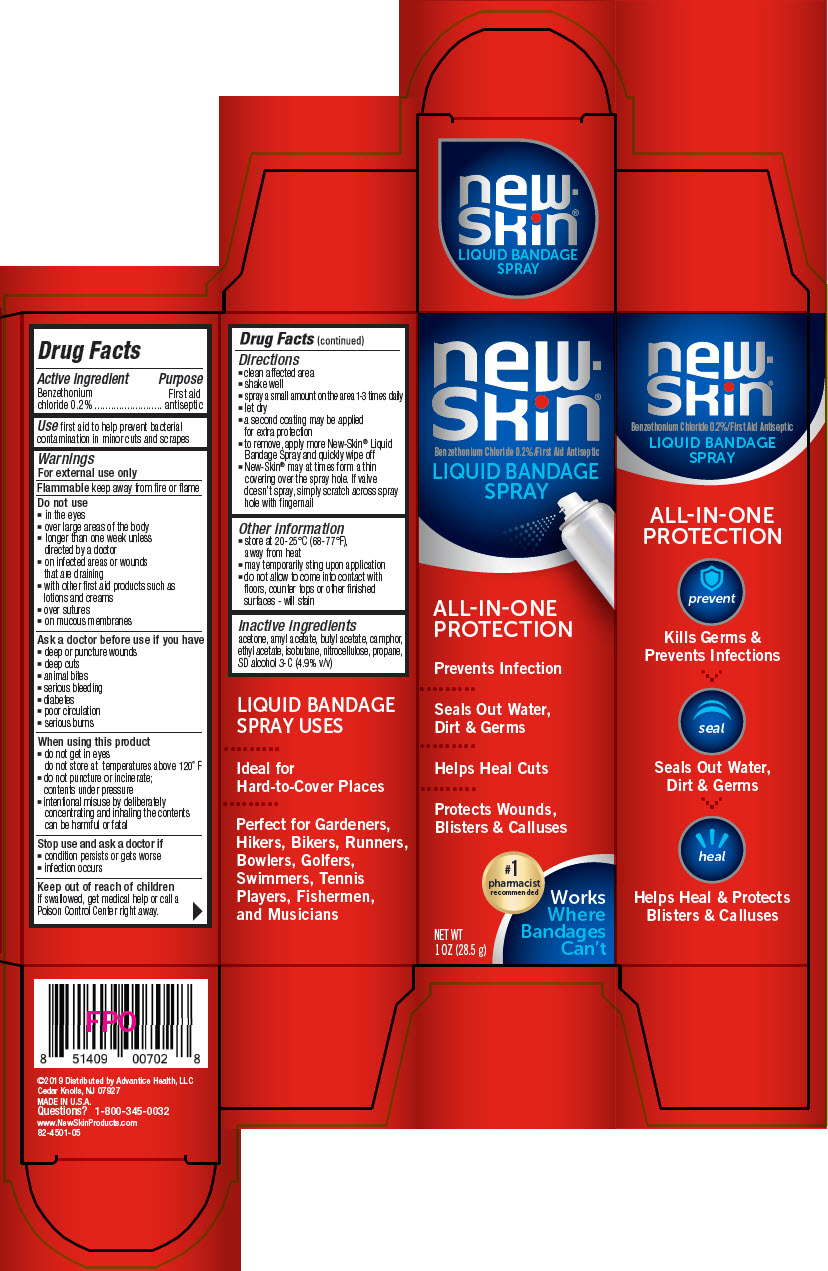 DRUG LABEL: New Skin Bandage
NDC: 16864-450 | Form: SPRAY
Manufacturer: Advantice Health, LLC.
Category: otc | Type: HUMAN OTC DRUG LABEL
Date: 20241212

ACTIVE INGREDIENTS: BENZETHONIUM CHLORIDE 60 mg/1 g
INACTIVE INGREDIENTS: ETHYL ACETATE; ACETONE; BUTYL ACETATE; AMYL ACETATE; ALCOHOL; PYROXYLIN; CAMPHOR (NATURAL); ISOBUTANE; PROPANE

New Skin Spray Bandage

Drug Facts

Active ingredient

Benzethonium chloride 0.2%

Purpose

First aid antiseptic

Use

first aid to help prevent bacterial contamination in minor cuts and scrapes

Warnings

For external use only

Flammablekeep away from fire or flame

Do not use

- in the eyes
- over large areas of the body
- longer than one week unless directed by a doctor
- on infected areas or wounds that are draining
- with other first aid products such as lotions and creams
- over sutures
- on mucous membranes

Ask a doctor before use if you have

- deep or puncture wounds
- deep cuts
- animal bites
- serious bleeding
- diabetes
- poor circulation
- serious burns

When using this product

- do not get in eyes
- do not store at temperatures above 120° F
- do not puncture or incinerate; contents under pressure
- intentional misuse by deliberately concentrating and inhaling the contents can be harmful or fatal

Stop use and ask a doctor if

- condition persists or gets worse
- infection occurs

Keep out of reach of children

If swallowed, get medical help or call a Poison Control Center right away.

Directions

- clean affected area
- shake well
- spray a small amount on the area 1-3 times daily
- let dry
- a second coating may be applied for extra protection
- to remove, apply more New-Skin®Liquid Bandage Spray and quickly wipe off
- New-Skin®may at times form a thin covering over the spray hole. If valve doesn't spray, simply scratch across spray hole with fingernail

Other information

- store at 20-25°C (68-77°F), away from heat
- may temporarily sting upon application
- do not allow to come into contact with floors, counter tops or other finished surfaces - will stain

Inactive ingredients

acetone, amyl acetate, butyl acetate, camphor, ethyl acetate, isobutane, nitrocellulose, propane, SD alcohol 3-C (4.9% v/v)

Questions?

1-800-345-0032
www.NewSkinProducts.com

Distributed by Advantice Health, LLC
Cedar Knolls, NJ 07927

PRINCIPAL DISPLAY PANEL - 28.5 g Canister Box

new-
skin®
Benzethonium Chloride 0.2%/First Aid Antiseptic
LIQUID BANDAGE
SPRAY

ALL-IN-ONE
PROTECTION

Prevents Infection

Seals Out Water,
Dirt & Germs

Helps Heal Cuts

Protects Wounds,
Blisters & Calluses

#1
pharmacist
recommended

NET WT
1 OZ (28.5 g)

Works
Where
Bandages
Can't